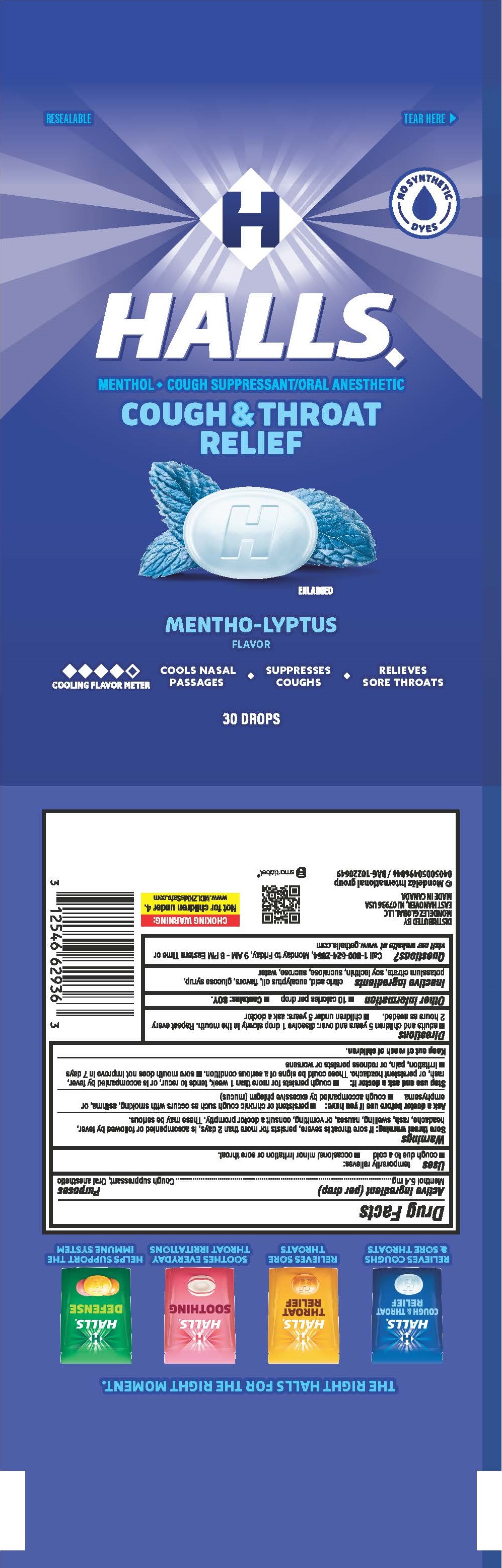 DRUG LABEL: HALLS
NDC: 12546-116 | Form: LOZENGE
Manufacturer: Mondelez Global LLC
Category: otc | Type: HUMAN OTC DRUG LABEL
Date: 20250702

ACTIVE INGREDIENTS: MENTHOL 5.4 mg/1 1
INACTIVE INGREDIENTS: LECITHIN, SOYBEAN; SUCROSE; WATER; ANHYDROUS CITRIC ACID; CORN SYRUP; SUCRALOSE; EUCALYPTUS OIL; POTASSIUM CITRATE

Active Ingredient

<(per drop) Menthol 5.4 mg>

Purposes

<Cough Suppressant, Oral Anesthetic>

Uses

<temporarily relieves:>

- cough due to a cold
- occasional minor irritation or sore throat

Warnings

< Sore throat warning: if sore throat is severe, persists for more than 2 days, is accompanied by fever, headache, rash, swelling, or vomiting, consult a doctor promptly. These may be serious.>

Ask a doctor before use if you have

- persistent or chronic cough such as occurs with smoking, asthma, or emphysema
- cough accompanied by excessive phlegm (mucus)

Stop use and ask a doctor if

- cough persists for more than 1 week, tends to recur, or is accompanied by fever, rash, or persistent headache. These could be signs of a serious condition.
- sore mouth does not improve in 7 days
- irritation, pain, or redness persists or worsens

Directions

- adults and children 5 years and over: dissolve 1 drop slowly in the mouth. Repeat every 2 hours as needed.
- children under 5 years: ask a doctor

Other information

- 10 calories per drop
- Contains: SOY.

Inactive ingredients

<citric acid, eucalyptus oil, flavors, glucose syrup, potassium citrate, soy lecithin, sucralose, sucrose, water>

Questions

<Call 1-800-524-2854, Monday to Friday, 9AM-6PM Eastern Time or visit our website at www.gethalls.com>